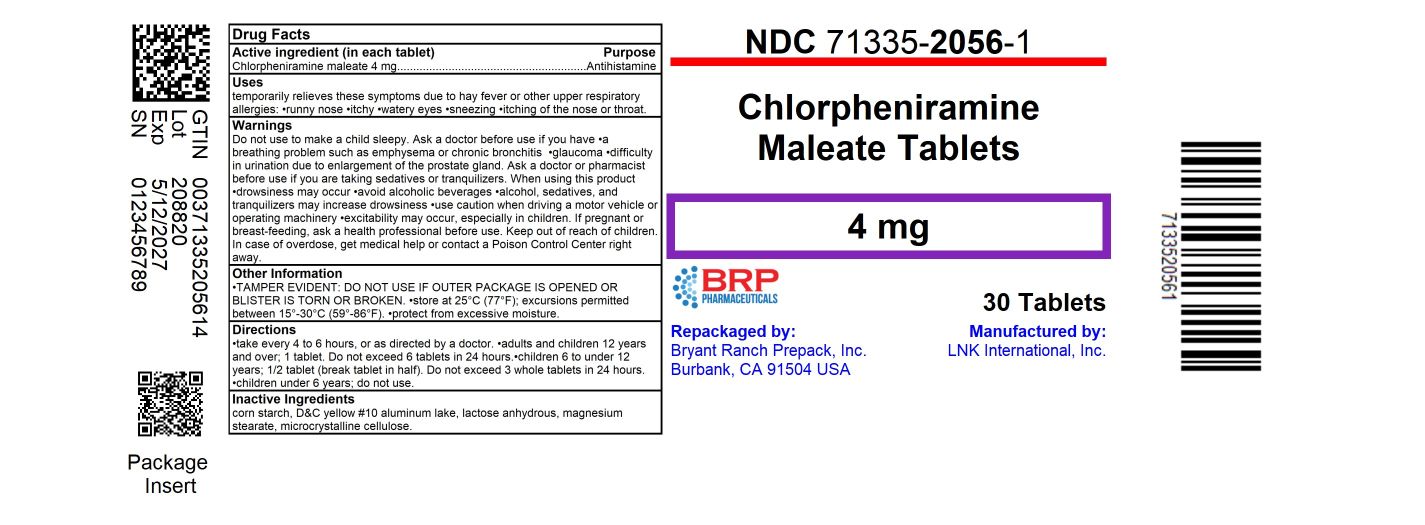 DRUG LABEL: Allergy
NDC: 71335-2056 | Form: TABLET
Manufacturer: Bryant Ranch Prepack
Category: otc | Type: HUMAN OTC DRUG LABEL
Date: 20250512

ACTIVE INGREDIENTS: CHLORPHENIRAMINE MALEATE 4 mg/1 1
INACTIVE INGREDIENTS: STARCH, CORN; D&C YELLOW NO. 10 ALUMINUM LAKE; ANHYDROUS LACTOSE; MAGNESIUM STEARATE; MICROCRYSTALLINE CELLULOSE

Major 44-194

Active ingredient (in each tablet)

Chlorpheniramine maleate 4 mg

Purpose

Antihistamine

Uses

temporarily relieves these symptoms due to hay fever or other upper respiratory allergies:

- runny nose
- itchy, watery eyes
- sneezing
- itching of the nose or throat

Warnings

Do not use

to make a child sleepy.

Ask a doctor before use if you have

- a breathing problem such as emphysema or chronic bronchitis
- glaucoma
- difficulty in urination due to enlargement of the prostate gland

Ask a doctor or pharmacist before use if you are

taking sedatives or tranquilizers.

When using this product

- drowsiness may occur
- avoid alcoholic beverages
- alcohol, sedatives, and tranquilizers may increase drowsiness
- use caution when driving a motor vehicle or operating machinery
- excitability may occur, especially in children

If pregnant or breast-feeding,

ask a health professional before use.

Keep out of reach of children.

In case of overdose, get medical help or contact a Poison Control Center right away.

Directions

- take every 4 to 6 hours, or as directed by a doctor

adults and children 12 years and over | 1 tablet. Do not exceed 6 tablets in 24 hours.
children 6 to under 12 years | 1/2 tablet (break tablet in half). Do not exceed 3 whole tablets in 24 hours.
children under 6 years | do not use

Other information

- TAMPER EVIDENT: DO NOT USE IF OUTER PACKAGE IS OPENED OR BLISTER IS TORN OR BROKEN
- store at 25°C (77°F); excursions permitted between 15°-30°C (59°-86°F)
- protect from excessive moisture
- see end flap for expiration date and lot number

Inactive ingredients

corn starch, D&C yellow #10 aluminum lake, lactose anhydrous, magnesium stearate, microcrystalline cellulose

Questions or comments?

1-800-426-9391

HOW SUPPLIED

Chlorpheniramine Maleate 4 mg

- NDC 71335-2056-1: 30 Tablets in a BOTTLE
- NDC 71335-2056-2: 60 Tablets in a BOTTLE
- NDC 71335-2056-3: 100 Tablets in a BOTTLE
- NDC 71335-2056-4: 120 Tablets in a BOTTLE
- NDC 71335-2056-5: 40 Tablets in a BOTTLE
- NDC 71335-2056-6: 24 Tablets in a BOTTLE

Repackaged/Relabeled by:
Bryant Ranch Prepack, Inc.
Burbank, CA 91504

PACKAGE LABEL

Chlorpheniramine Maleate 4mg Tablet